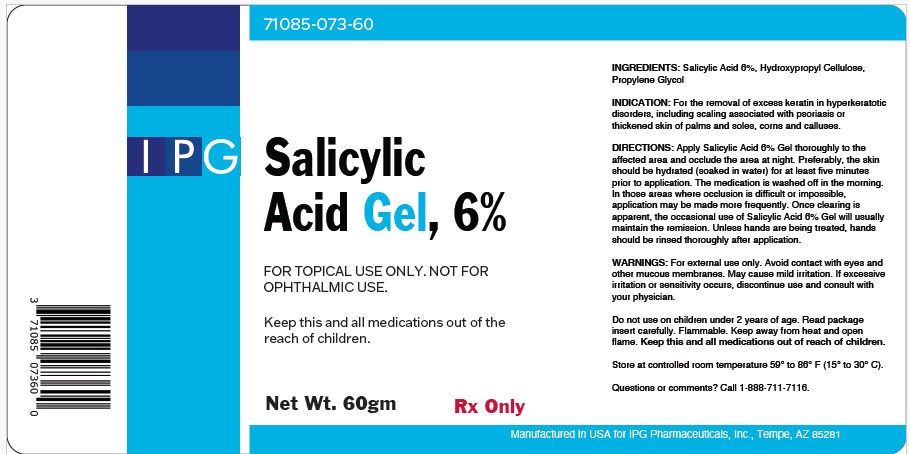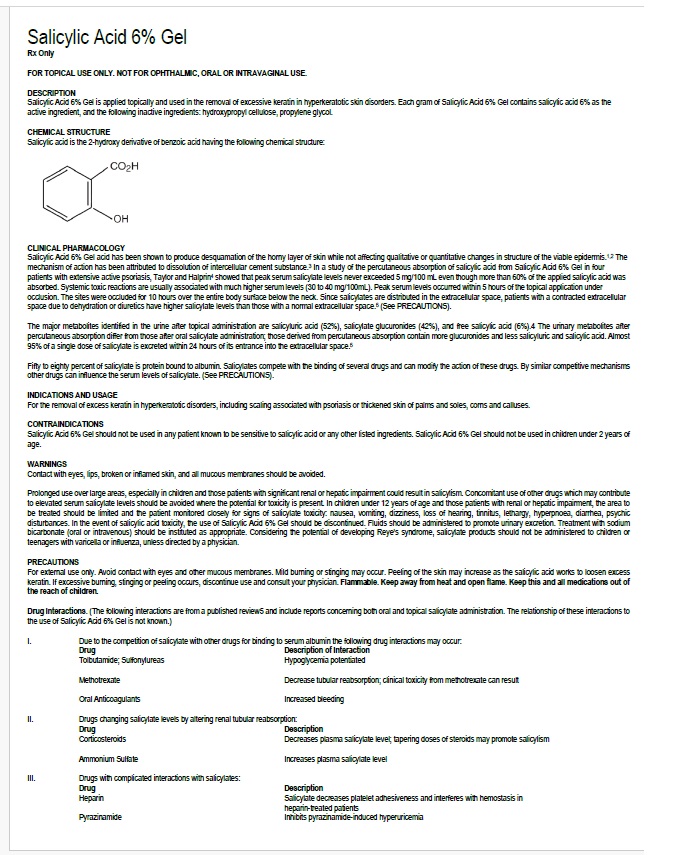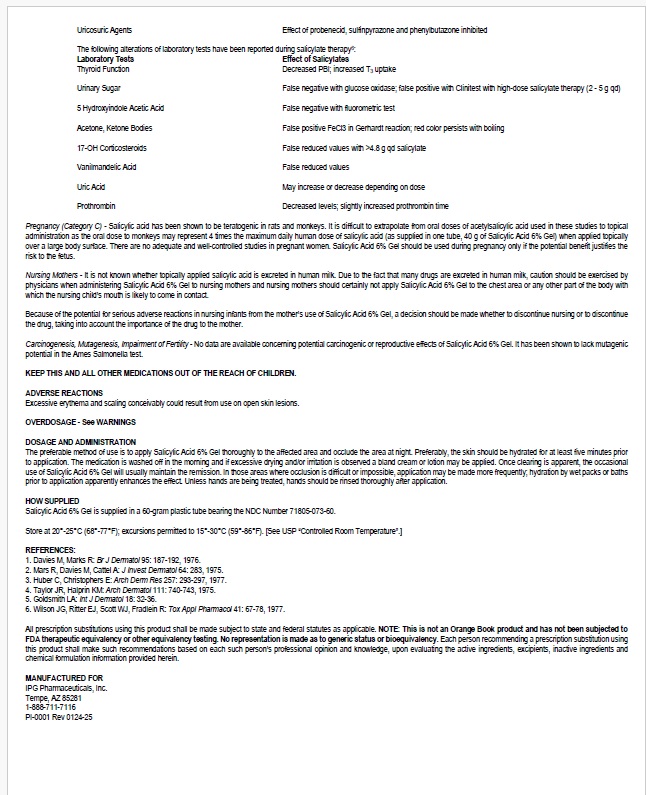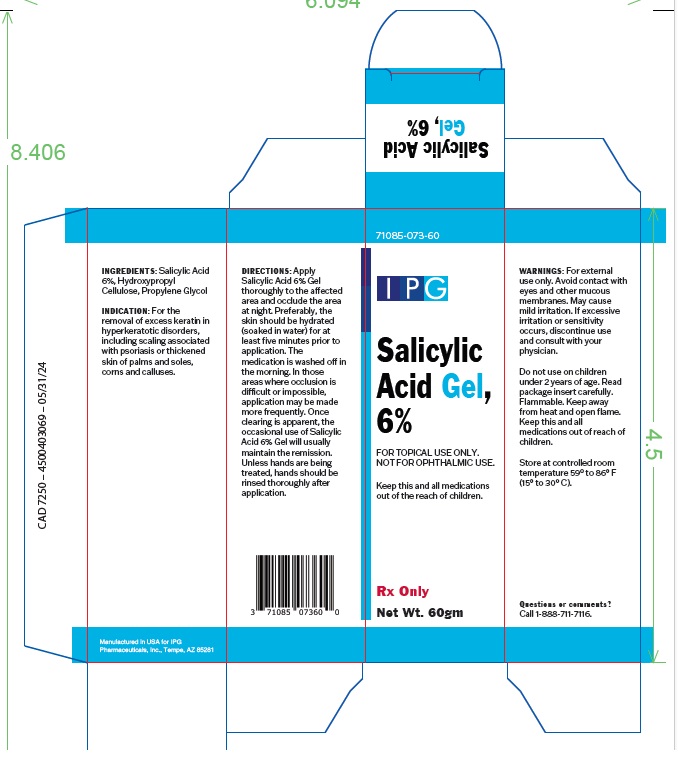 DRUG LABEL: Salicylic Acid 6% Gel
NDC: 71085-073 | Form: GEL
Manufacturer: IPG PHARMACEUTICALS, INC.
Category: prescription | Type: HUMAN PRESCRIPTION DRUG LABEL
Date: 20250121

ACTIVE INGREDIENTS: SALICYLIC ACID 6 g/100 g
INACTIVE INGREDIENTS: HYDROXYPROPYL CELLULOSE, UNSPECIFIED; PROPYLENE GLYCOL

Active Ingredient

Salicylic Acid 6%

Uses

For the removal of excess keratin in hyperkeratotic disorders, including scaling associated with psoriasis or thickened skin of palms and soles, corns and calluses.

Directions

Apply Salicylic Acid 6% Gel thoroughly to the affected area and occlude the area at night. Preferably, the skin should be hydrated (soaked in water) for at least five minutes prior to application. The medication is washed off in the morning. In those areas where occlusion is difficult or impossible, application may be made more frequently. Once clearing is apparent, the occasional use of Salicylic Acid 6% Gel will usually
maintain the remission. Unless hands are being treated, hands should be rinsed thoroughly after application.

Warning

For external use only. Avoid contact with eyes and other mucous membranes. May cause mild irritation. If excessive irritation or sensitivity occurs, discontinue use and consult with your physician. Do not use on children under 2 years of age. Read package insert carefully. Flammable. Keep away from heat and open flame. Keep this and all medications out of reach of children.

Other Information

Store at controlled room temperature 59° to 86° F (15° to 30° C).

Questions or comments? Call 1-888-711-7116.

Inactive ingredient

Hydroxypropyl Cellulose, Propylene Glycol